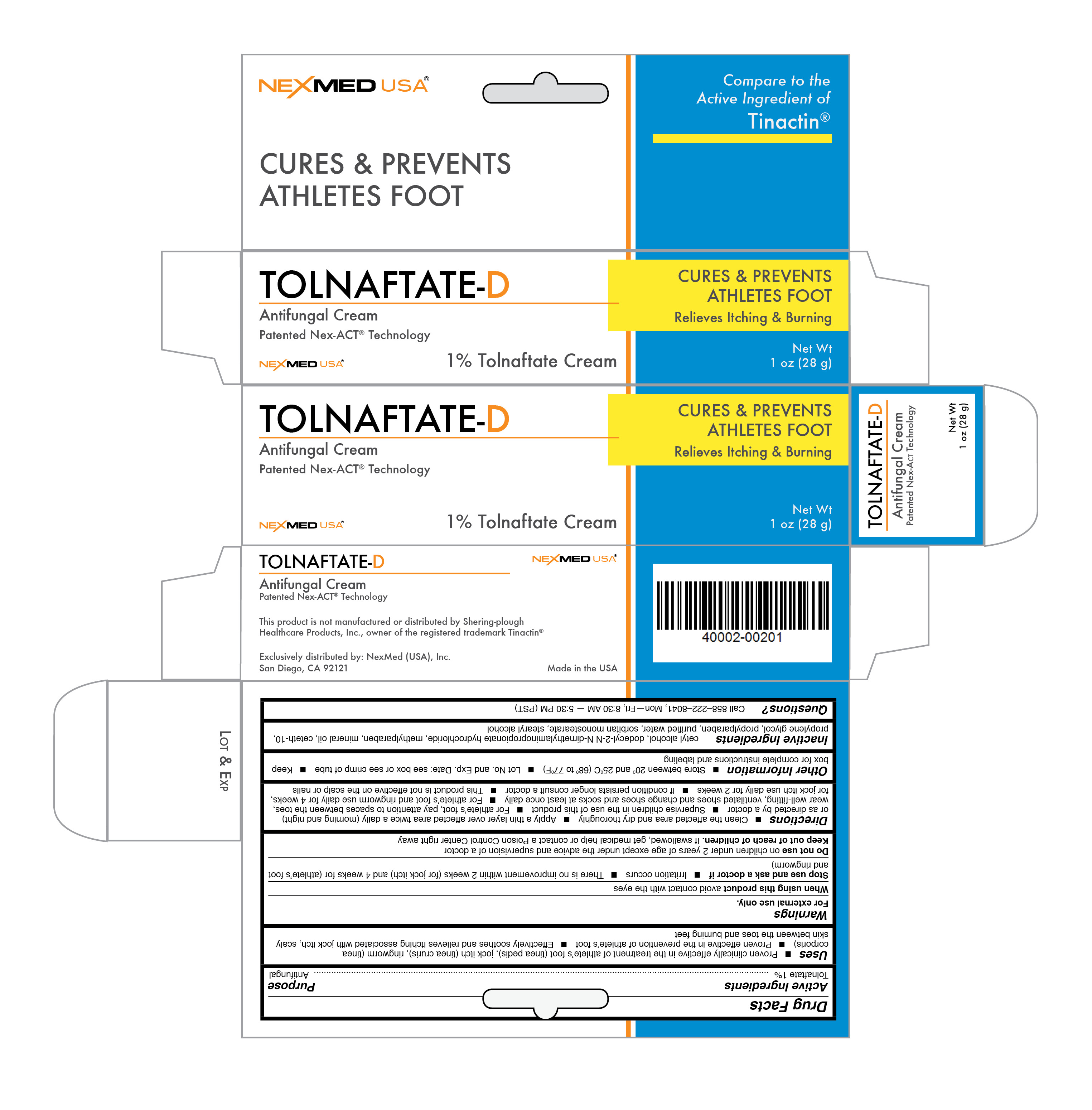 DRUG LABEL: Tolnaftate
NDC: 40002-002 | Form: CREAM
Manufacturer: NexMed (USA), Inc.
Category: otc | Type: HUMAN OTC DRUG LABEL
Date: 20110816

ACTIVE INGREDIENTS: Tolnaftate 1 g/100 g
INACTIVE INGREDIENTS: Cetyl Alcohol; Dodecyl-2-N,N-Dimethylaminopropionate Hydrochloride; Methylparaben; Mineral Oil; Ceteth-10; Propylene Glycol; Propylparaben; Water; Sorbitan Monostearate; Stearyl Alcohol

Drug Facts

Active Ingredient

Tolnaftate

Purpose

Antifungal

Uses

- Proven clinically effective in the treatment of athlete’s foot (tinea pedis), jock itch (tinea cruris), ringworm (tinea corporis)
- Proven effective in the prevention of athlete’s foot
- Effectively soothes and relieves itching associated with jock itch, scaly skin between the toes and burning feet

Warnings

For external use only

When using this product

avoid contact with the eyes

Stop use and ask a doctor if

- Irritation occurs
- There is no improvement within 2 weeks (for jock itch) and 4 weeks for (athlete’s foot and ringworm)

Do not use

on children under 2 years of age except under the advice and supervision of a doctor

Keep out of reach of children

If swallowed, get medical help or contact a Poison Control Center right away

Directions

- Clean the affected area and dry thoroughly
- Apply a thin layer over affected area twice a daily (morning and night) or as directed by a doctor
- Supervise children in the use of this product
- For athlete’s foot, pay attention to spaces between the toes, wear well-fitting, ventilated shoes and change shoes and socks at least once daily
- For athlete’s foot and ringworm use daily for 4 weeks, for jock itch use daily for 2 weeks.
- If condition persists longer consult a doctor
- This product is not effective on the scalp or nails

Other information

- Store between 20⁰ and 25⁰C (68⁰ to 77⁰F)
- Lot No. and Exp. Date: see box or see crimp of tube
- Keep box for complete instructions and labeling

Inactive Ingredients

cetyl alcohol, dodecyl-2-N N-dimethylaminopropionate hydrochloride, methylparaben, mineral oil, ceteth-10, propylene glycol, propylparaben, purified water, sorbitan monostearate, stearyl alcohol

Questions?

Call 858-222-8041, Mon-Fri, 8:30 AM - 5:30PM (PST)